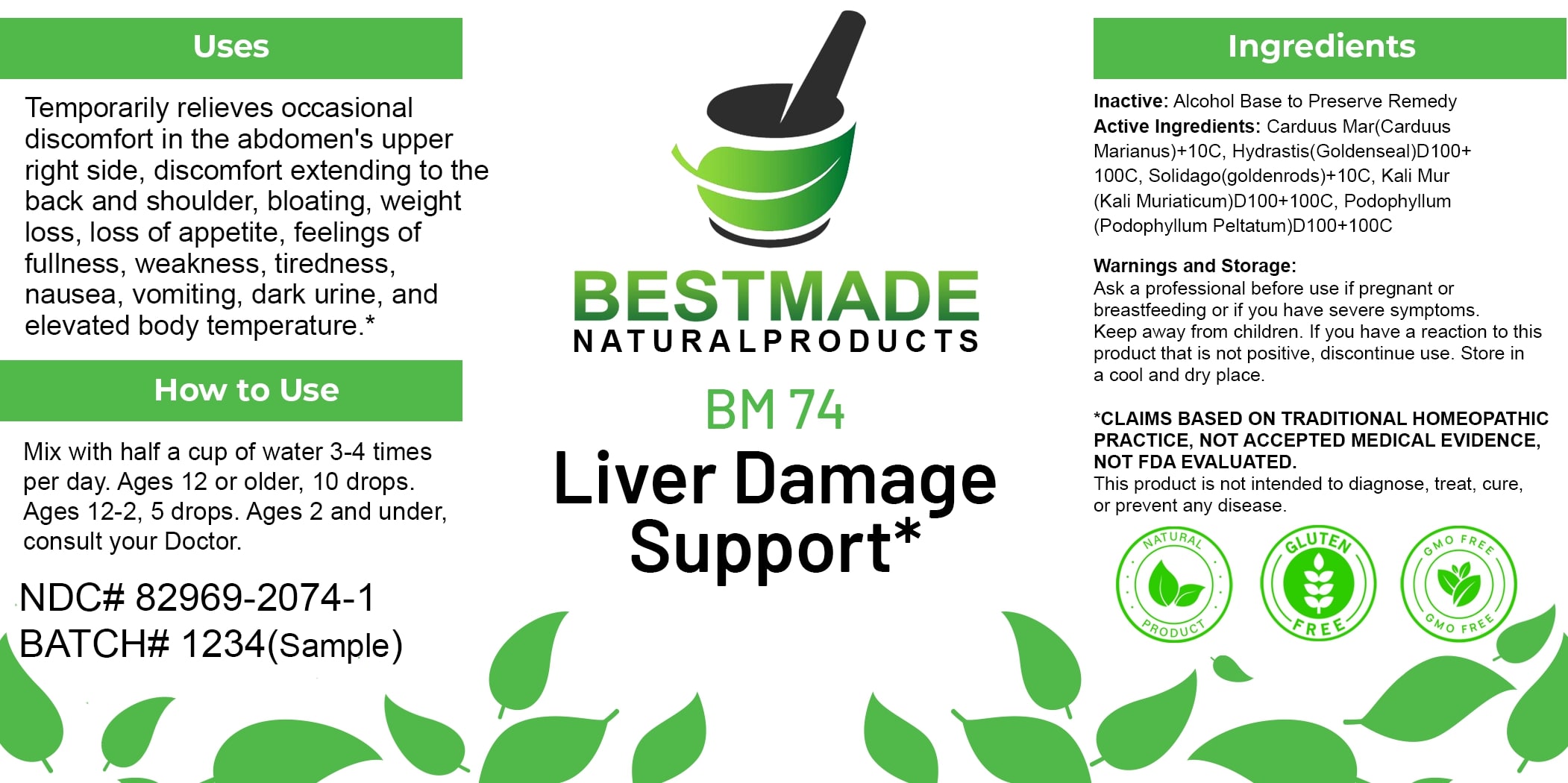 DRUG LABEL: Bestmade Natural Products BM74
NDC: 82969-2074 | Form: LIQUID
Manufacturer: Bestmade Natural Products
Category: homeopathic | Type: HUMAN OTC DRUG LABEL
Date: 20250130

ACTIVE INGREDIENTS: MILK THISTLE 30 [hp_C]/30 [hp_C]; GOLDENSEAL 30 [hp_C]/30 [hp_C]; SOLIDAGO VIRGAUREA FLOWERING TOP 30 [hp_C]/30 [hp_C]; PODOPHYLLUM PELTATUM ROOT 30 [hp_C]/30 [hp_C]; POTASSIUM CHLORIDE 30 [hp_C]/30 [hp_C]
INACTIVE INGREDIENTS: ALCOHOL 30 [hp_C]/30 [hp_C]

BM74

DOSAGE AND ADMINISTRATION

How to Use

Mix with half a cup of water 3-4 times per day. Ages 12 or older, 10 drops. Ages 12-2, 5 drops. Ages 2 and under, consult your Doctor.

INACTIVE INGREDIENT

Ingredients

Inactive: Alcohol Base to Preserve Remedy

ACTIVE INGREDIENT

Active Ingredients: Carduus Mar(Carduus Marianus)+10C, Hydrastis(Goldensea)D100+100C, Solidago(goldenrods)+10C, Kali Mur (Kali Muriaticum)D100+100C, Podophyllum (Podophyllum Peltatum)D100+100C

Uses

Temporarily relieves occasional discomfort in the abdomen's upper right side, discomfort extending to the back and shoulder, bloating, weight loss, loss of appetite, feelings of fullness, weakness, tiredness, nausea, vomiting, dark urine, and elevated body temperature.*

*CLAIMS BASED ON TRADITIONAL HOMEOPATHIC PRACTICE, NOT ACCEPTED MEDICAL EVIDENCE, NOT FDA EVALUATED.

This product is not intended to diagnose, treat, cure, or prevent any disease.

Uses

Temporarily relieves occasional discomfort in the abdomen's upper right side, discomfort extending to the back and shoulder, bloating, weight loss, loss of appetite, feelings of fullness, weakness, tiredness, nausea, vomiting, dark urine, and elevated body temperature.*

*CLAIMS BASED ON TRADITIONAL HOMEOPATHIC PRACTICE, NOT ACCEPTED MEDICAL EVIDENCE, NOT FDA EVALUATED.

This product is not intended to diagnose, treat, cure, or prevent any disease.

KEEP OUT OF REACH OF CHILDREN

Warnings and Storage:

Ask a professional before use if pregnant or breastfeeding or if you have severe symptoms. Keep away from children. If you have a reaction to this product that is not positive, discontinue use. Store in a cool and dry place.

Warnings and Storage:

Ask a professional before use if pregnant or breastfeeding or if you have severe symptoms. Keep away from children. If you have a reaction to this product that is not positive, discontinue use. Store in a cool and dry place.

*CLAIMS BASED ON TRADITIONAL HOMEOPATHIC PRACTICE, NOT ACCEPTED MEDICAL EVIDENCE, NOT FDA EVALUATED.

This product is not intended to diagnose, treat, cure, or prevent any disease.

Entire package label